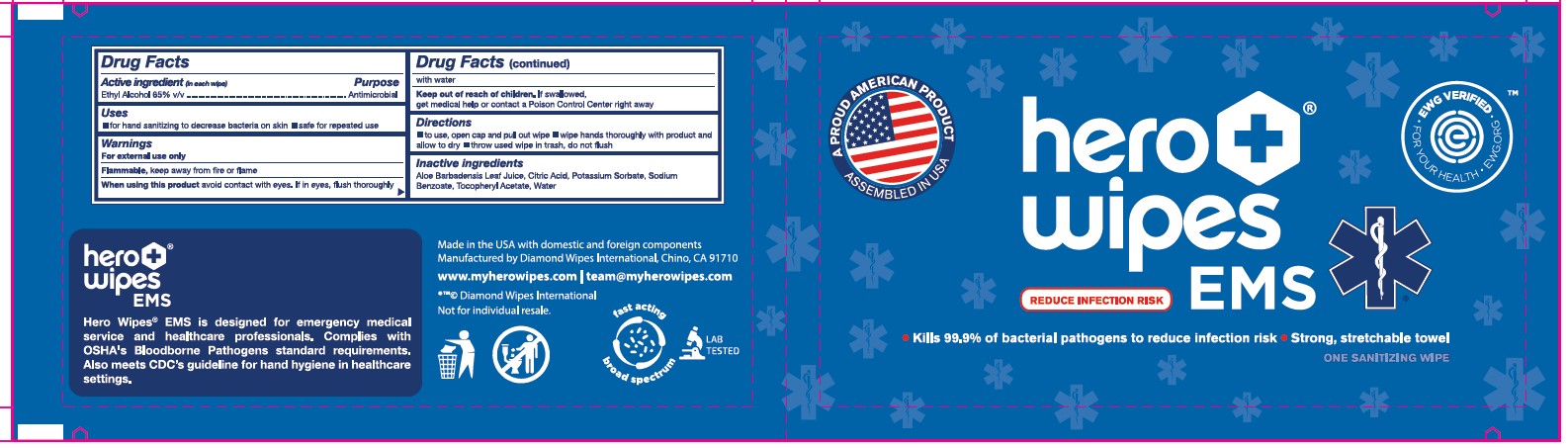 DRUG LABEL: Hero Wipes EMS
NDC: 64709-256 | Form: CLOTH
Manufacturer: Diamond Wipes International, Inc
Category: otc | Type: HUMAN OTC DRUG LABEL
Date: 20231204

ACTIVE INGREDIENTS: ALCOHOL 65 mL/100 mL
INACTIVE INGREDIENTS: .ALPHA.-TOCOPHEROL ACETATE; WATER; ALOE VERA LEAF; SODIUM BENZOATE; ANHYDROUS CITRIC ACID; POTASSIUM SORBATE

Hero Wipes EMS

Active Ingredients (in each wipe)

Ethyl Alcohol 65% v/v

Purpose

Antimicrobial

Uses

for hand sanitizing to decrease bacteria on skin

safe for repeated use

Warnings

For external use only.

Flammable, keep away from fire or flame.

When using this product avoid contact with eyes. If in eyes, flush thoroughly with water.

Keep out of reach of children. If swallowed, get medical help or contact a Poison Control Center right away.

Directions

- to use, open cap and pull out wipe
- wipe hands thoroughly with product and allow to dry
- throw used wipe in trash, do not flush

Inactive ingredients

Aloe Barbadensis Leaf Juice, Citric Acid, Potassium Sorbate, Sodium Benzoate, Tocopheryl Acetate, Water

Label info

Front panel

A PROUD AMERICAN PRODUCT ASSEMBLED IN USA

hero wipes EMA

EWG VRETIFIED FOR YOUR HEALTH EWG.ORG

REDUCE INFECTION RISK

Kills 99.9% of bacterial pathogens to reduce infection risk

Strong, stretchable towel

Back panel

Drug facts box

hero wipes EMS

Hero Wipes EMS is designed for emergency medical service and healthcare professionals. Complies with OSHA's Bloodborne Pathogens standard requirements. Also meets CDC's guideline for hand hyiene in healthcare settings.

Made in the USA with domestic and goreign components.

Manufactured by Diamond Wipes International, Chino, CA91710

www.myherowipes.com | team@myherowipes.com

Diamond Wipes International

Not for individual resale

fast acting

broad spectrum

LAB TESTED